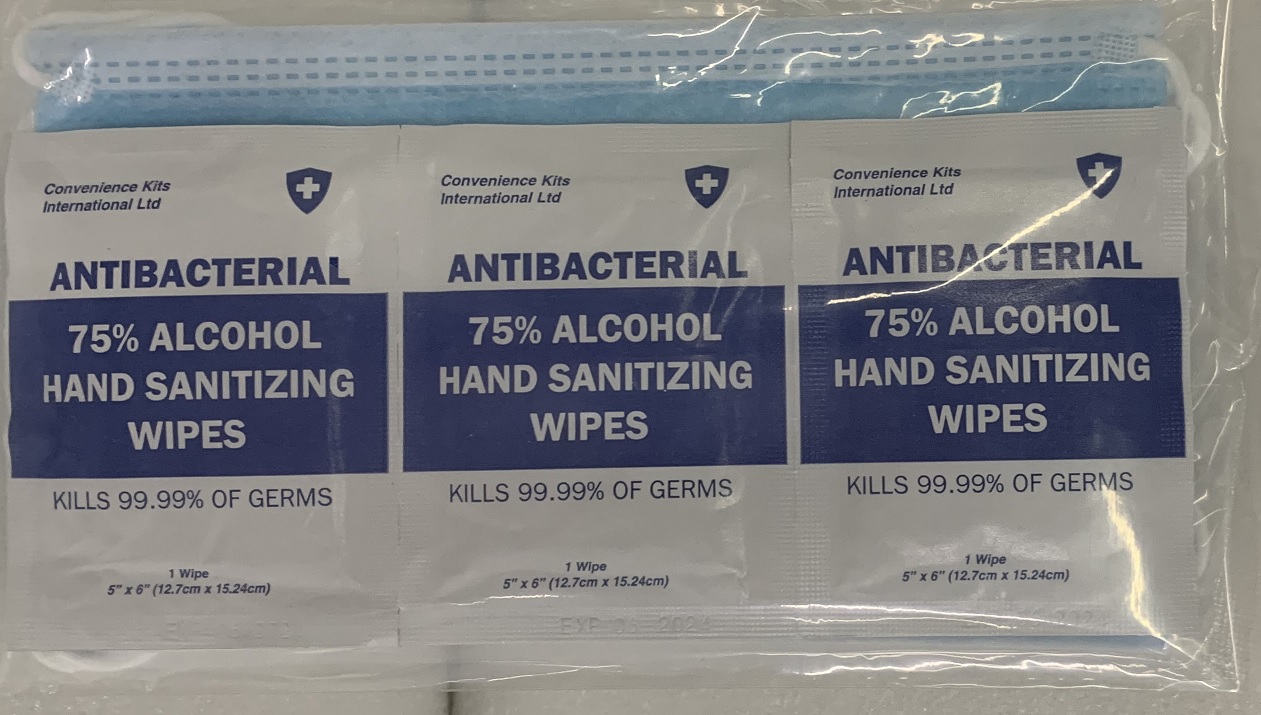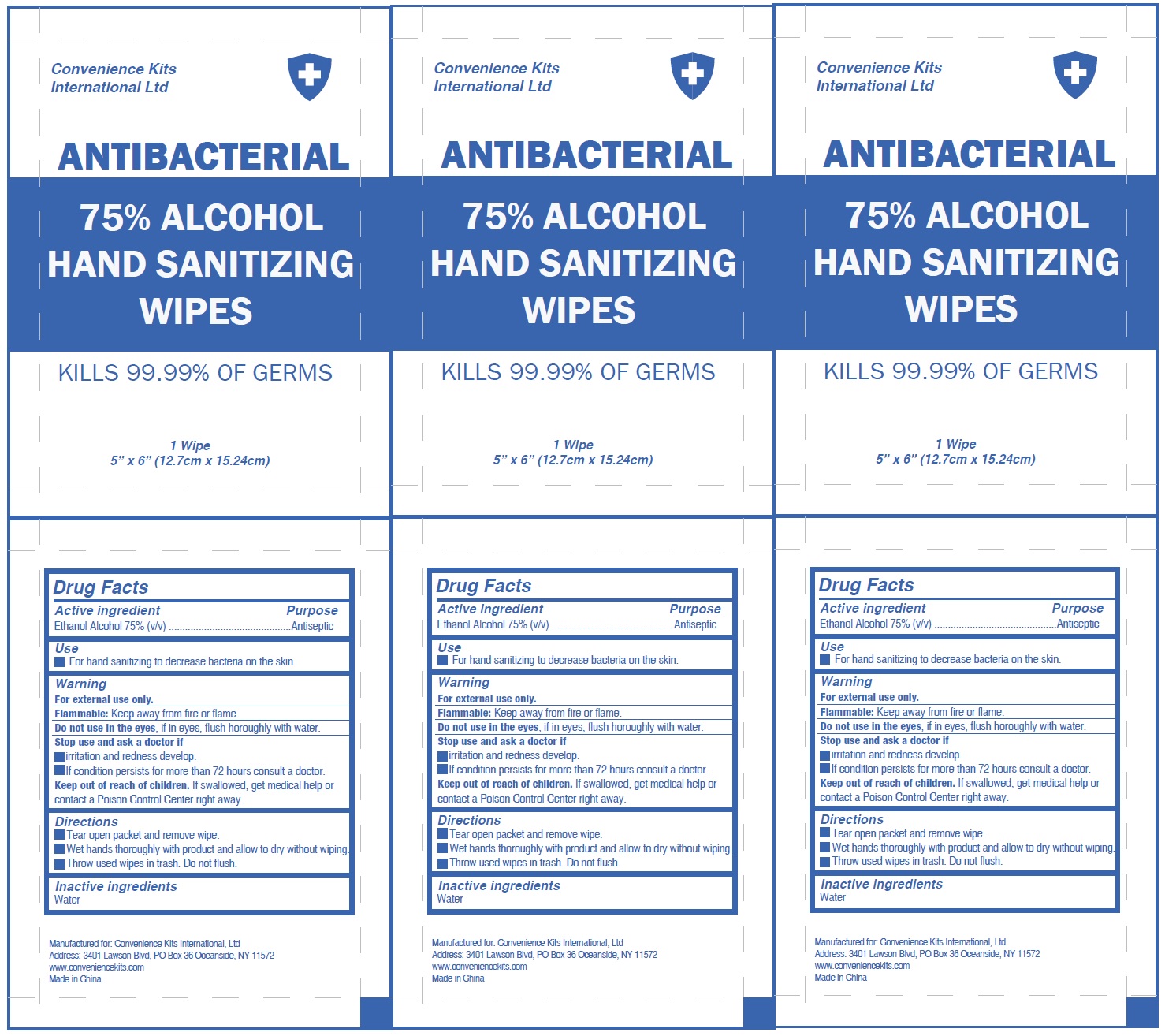 DRUG LABEL: Antibacterial Hand Sanitizing 3 Wipes and 2 non-medical masks
NDC: 82158-003 | Form: KIT | Route: TOPICAL
Manufacturer: Convenience Kits International Ltd
Category: otc | Type: HUMAN OTC DRUG LABEL
Date: 20231026

ACTIVE INGREDIENTS: ALCOHOL 75 mL/100 mL
INACTIVE INGREDIENTS: WATER

Antibacterial Hand Sanitizing 3 Wipes and 2 non-medical masks

Active ingredient

Ethanol Alcohol 75% (v/v)

Purpose

Antiseptic

Use

- For hand sanitizing to decrease bacteria on the skin.

Warning

For external use only.

Keep away from fire or flame. Flammable:

Do not use

in the eyes, if in eyes, flush horoughly with water.

Stop use and ask a doctor if

- irritation and redness develop.
- If condition persists for more than 72 hours consult a doctor.

Keep out of reach of children.

If swallowed, get medical help or contact a Poison Control Center right away.

Directions

- Tear open packet and remove wipe.
- Wet hands thoroughly with product and allow to dry without wiping.
- Throw used wipes in trash. Do not flush.

Inactive ingredients

Water